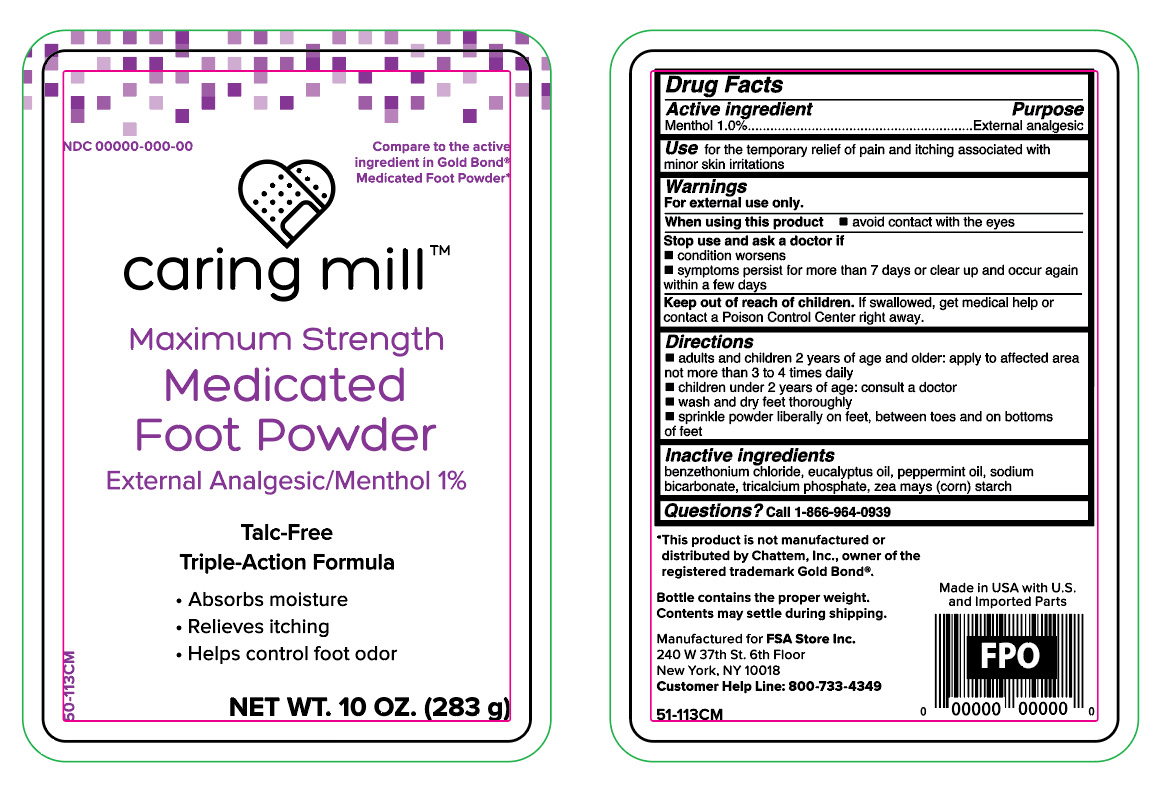 DRUG LABEL: Menthol
NDC: 81522-069 | Form: POWDER
Manufacturer: FSA Store Inc.
Category: otc | Type: HUMAN OTC DRUG LABEL
Date: 20251027

ACTIVE INGREDIENTS: MENTHOL 10 mg/1 g
INACTIVE INGREDIENTS: ZEA MAYS SUBSP. MAYS WHOLE; TRICALCIUM PHOSPHATE; SODIUM BICARBONATE; BENZETHONIUM CHLORIDE; EUCALYPTUS OIL; PEPPERMINT OIL

Caring Mill Medicated Foot Powder -Talc Free

Active ingredient

Menthol 1.0%

Purpose

External analgesic

Use

for the temporary relief of pain and itching associated with minor skin irritations

Warnings

For external use only.

When using this product

- avoid contact with eyes

Stop and consult a doctor if

- conditions worsens
- symptoms persists for more than 7 days or clear up and occur again within a few days

Keep out of reach of children.

If swallowed, get medical help or contact a Poison Control Center right away.

Directions

- adults and children 2 years of age and older, apply to affected area not more than 3 to 4 times daily
- children under 2 years of age, consult a doctor
- wash and dry feet thoroughly
- sprinkle powder liberally on feet, between toes and on bottoms of feet

Inactive ingredients

benzathonium Chloride, eucalyptus oil, peppermint oil, sodium bicarbonate, tricalcium phosphate, zea mays (corn) starch

Questions?

Call 1-866-964-0939

Principal Display Panel

Caring Mill

maximum strength

medicated

foot powder

external analgesic/menthol 1 %

talc- free

triple action formula

- absorbs moisture
- relieve itching
- helps control foot odor

NET WT 10 OZ (283 g)